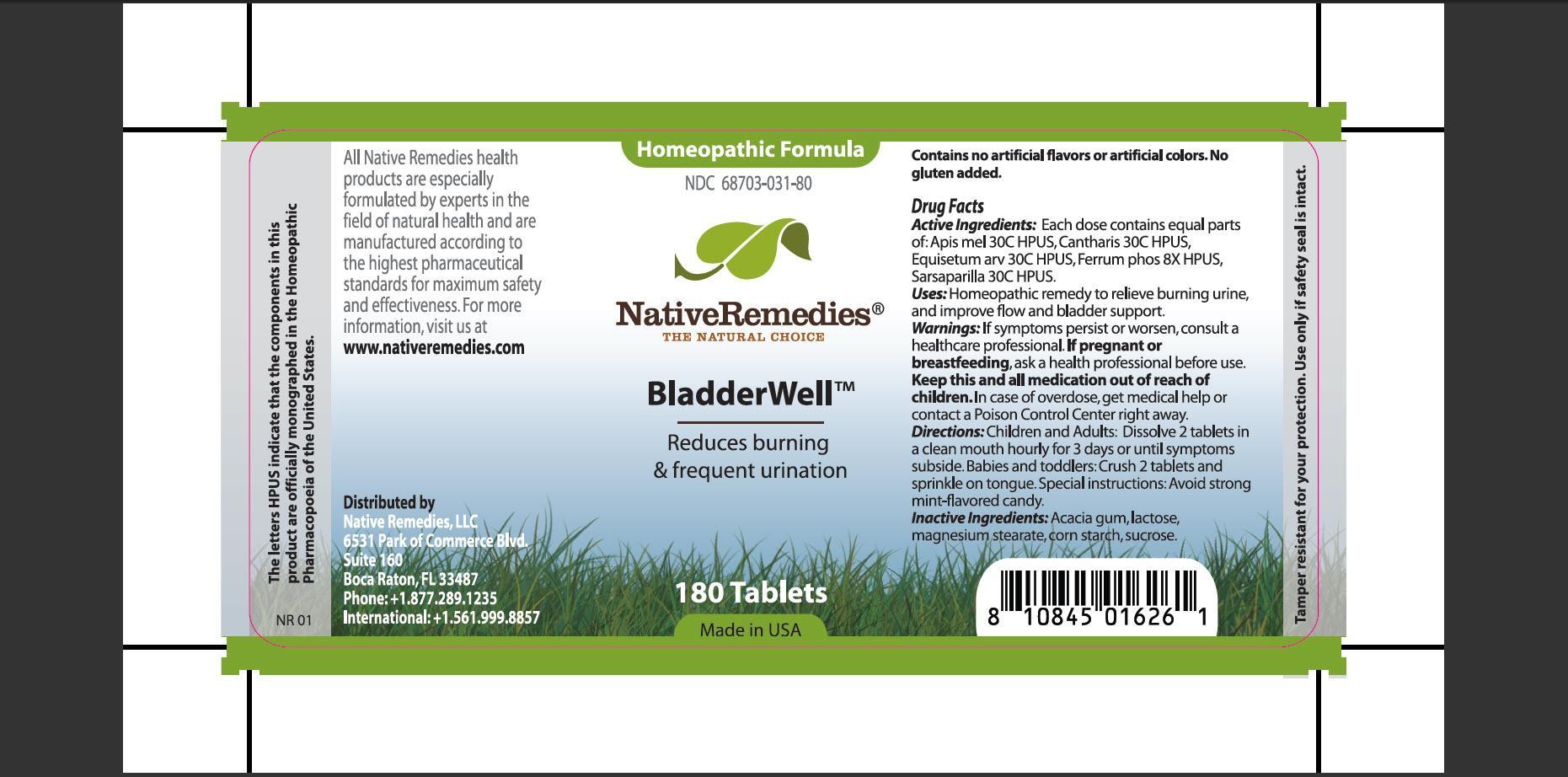 DRUG LABEL: BladderWell
NDC: 68703-031 | Form: TABLET
Manufacturer: Silver Star Brands, Inc
Category: homeopathic | Type: HUMAN OTC DRUG LABEL
Date: 20150716

ACTIVE INGREDIENTS: APIS MELLIFERA 30 [hp_C]/1 1; LYTTA VESICATORIA 30 [hp_C]/1 1; EQUISETUM ARVENSE TOP 30 [hp_C]/1 1; FERROSOFERRIC PHOSPHATE 8 [hp_X]/1 1; SMILAX REGELII ROOT 30 [hp_C]/1 1
INACTIVE INGREDIENTS: ACACIA; LACTOSE; MAGNESIUM STEARATE; STARCH, CORN; SUCROSE

BladderWell

PURPOSE

Reduces burning and frequent urination

ACTIVE INGREDIENT

Active Ingredients: Each dose contains equal parts of: Apis mel 30C HPUS, Cantharis 30C HPUS, Equisetum arv 30C HPUS, Ferrum phos 8X HPUS, Sarsaparilla 30C HPUS

INDICATIONS AND USAGE

Uses: Homeopathic remedy to relieve burning urine, and improve flow and bladder support

WARNINGS

Warnings: If symptoms persist or worsen, consult a healthcare professional

PREGNANCY OR BREAST FEEDING

If pregnant or breastfeeding, ask a health professional before use

KEEP OUT OF REACH OF CHILDREN

Keep this and all medication out of reach of children

OVERDOSAGE

In case of overdose, get medical help or contact a Poison COntrol Center right away

DOSAGE AND ADMINISTRATION

Directions: Children and adults: Dissolve 2 tablets in a clean mouth hourly for 3 days or until symptoms subside. Babies and toddlers: Crush 2 tablets and sprinkle on tongue. Special instructions: Avoid strong mint-flavored candy

INACTIVE INGREDIENT

Inactive Ingredients:Acacia gum, lactose, magnesium stearate, corn starch, sucrose

PATIENT COUNSELING INFORMATION

The letters HPUS indicate that the components in this products are oficially monographed in the Homeopathic Pharmacopoeia of the United States.

All Native Remedies health products are especially formulated by experts in the field of natural health and are manufactured according to the highest pharmaceutical standards for maximum safety and effectiveness. For more information, visit us at www.nativeremedies.com

Distributed by
Native Remedies, LLC
6531 Park of Commerce Blvd.
Suite 160
Boca Raton, Fl 33487
Phone:+1.877.289.1235
International: +1.561.999.8857

Contains no artificial flavors or artificial colors. No gluten added

STORAGE AND HANDLING

Tamper resistant for your protection. Use only if safety seal is intact